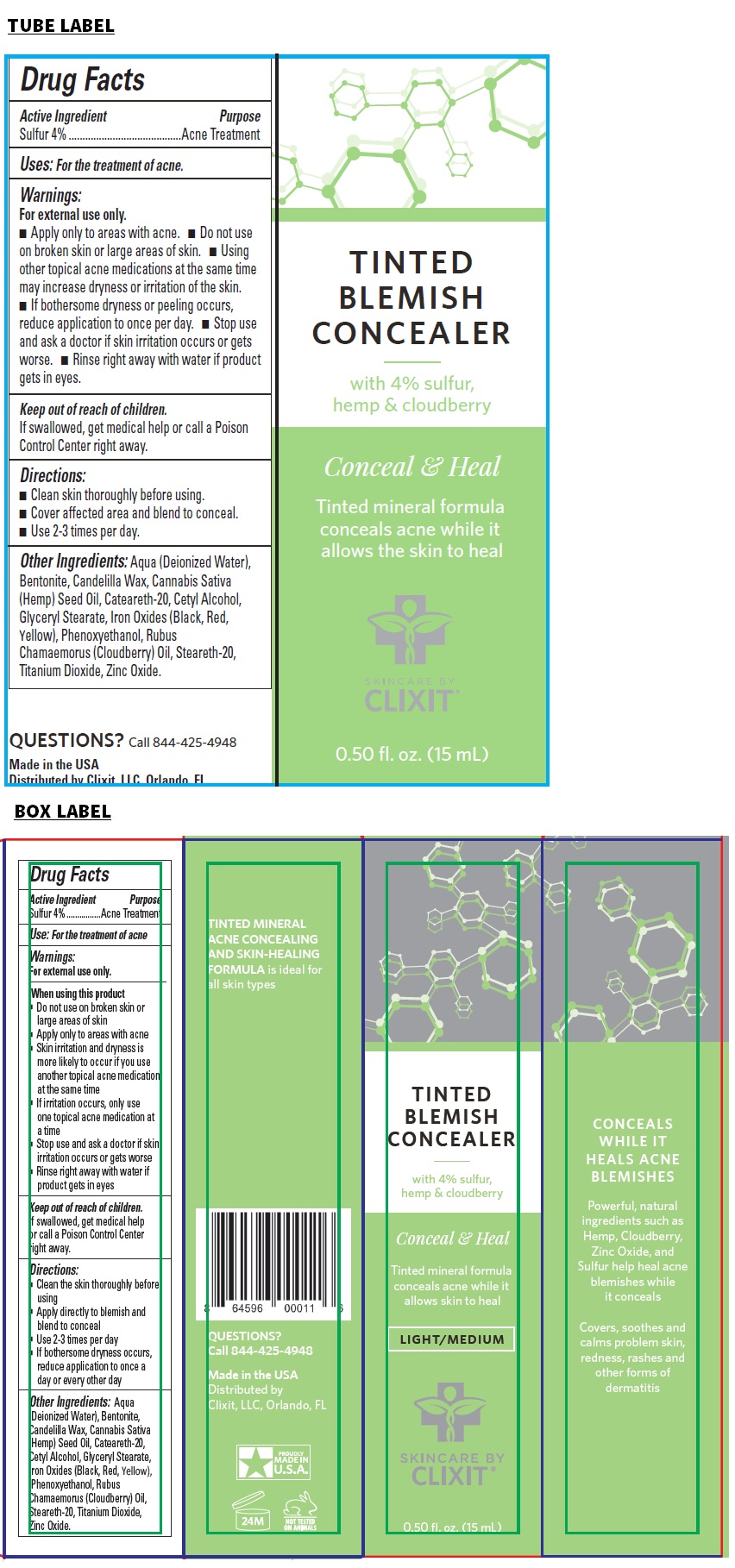 DRUG LABEL: CLIXIT TINTED BLEMISH CONCEALER
NDC: 71328-044 | Form: CREAM
Manufacturer: Clixit, Llc
Category: otc | Type: HUMAN OTC DRUG LABEL
Date: 20210417

ACTIVE INGREDIENTS: SULFUR 40 mg/1 mL
INACTIVE INGREDIENTS: WATER; BENTONITE; CANDELILLA WAX; CANNABIS SATIVA SEED OIL; POLYOXYL 20 CETOSTEARYL ETHER; CETYL ALCOHOL; GLYCERYL MONOSTEARATE; FERROSOFERRIC OXIDE; FERRIC OXIDE RED; FERRIC OXIDE YELLOW; PHENOXYETHANOL; RUBUS CHAMAEMORUS SEED OIL; STEARETH-20; TITANIUM DIOXIDE; ZINC OXIDE

CLIXIT® TINTED BLEMISH CONCEALER

Active Ingredient

Sulfur 4%

Purpose

Acne Treatment

Use:

For the treatment of acne

Warnings:

For external use only.

When using this product
• Do not use on broken skin or large areas of skin
• Apply only to areas with acne
• Skin irritation and dryness is more likely to occur if you use another topical acne medication at the same time
• If irritation occurs, only use one topical acne medication at a time
• Stop use and ask a doctor if skin irritation occurs or gets worse
• Rinse right away with water if product gets in eyes

Keep out of reach of children.
If swallowed, get medical help or call a Poison Control Center right away.

Directions:

• Clean the skin thoroughly before using
• Apply directly to blemish and blend to conceal
• Use 2-3 times per day
• If bothersome dryness occurs, reduce application to once a day or every other day

Other Ingredients:

Aqua (Deionized Water), Bentonite, Candelilla Wax, Cannabis Sativa (Hemp) Seed Oil, Ceteareth-20, Cetyl Alcohol, Glyceryl Stearate, Iron Oxides (Black, Red, Yellow), Phenoxyethanol, Rubus Chamaemorus (Cloudberry) Oil, Steareth-20, Titanium Dioxide, Zinc Oxide.

with 4% sulfur, hemp & cloudberry

Conceal & Heal

Tinted mineral formula conceals acne while it allows skin to heal

LIGHT/MEDIUM

SKINCARE BY CLIXIT®

CONCEALS WHILE IT HEALS ACNE BLEMISHES

Powerful, natural ingredients such as Hemp, Cloudberry, Zinc Oxide, and Sulfur help heal acne blemishes while it conceals

Covers, soothes and calms problem skin, redness, rashes and other forms of dermatitis

TINTED MINERAL ACNE CONCEALING AND SKIN-HEALING FORMULA is ideal for all skin types

QUESTIONS?
Call 844-425-4948

Made in the USA
Distributed by
Clixit, LLC, Orlando, FL

NOT TESTED ON ANIMALS